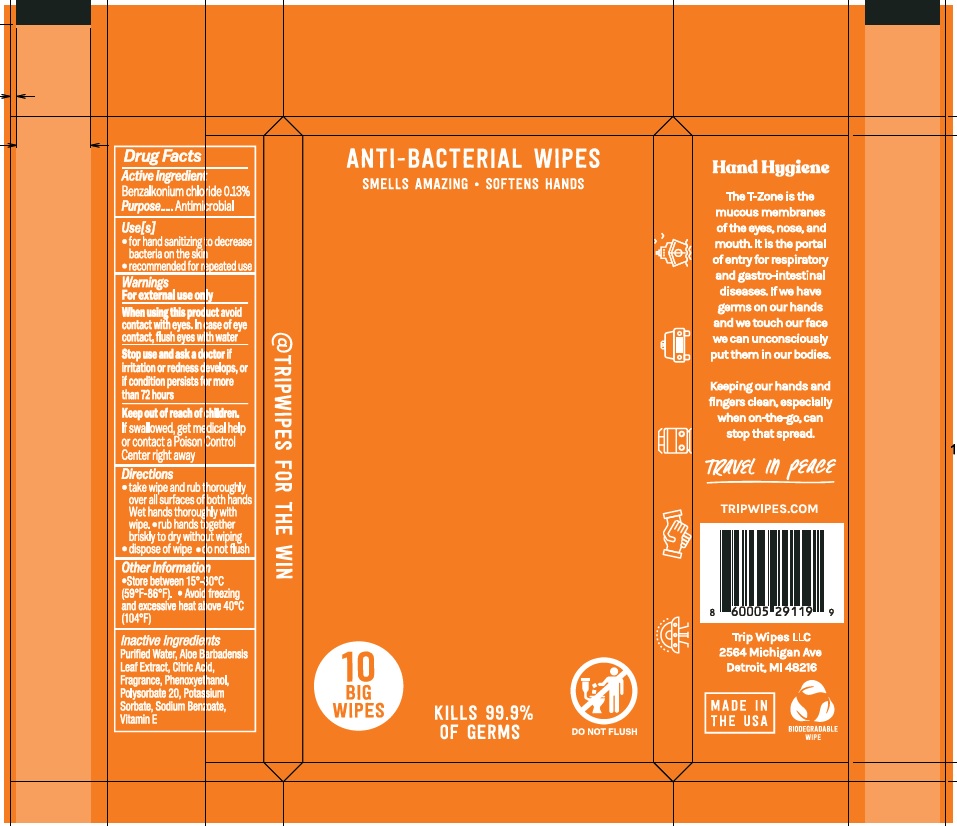 DRUG LABEL: Trip Wipes
NDC: 73030-025 | Form: CLOTH
Manufacturer: DETROIT WICK
Category: otc | Type: HUMAN OTC DRUG LABEL
Date: 20221213

ACTIVE INGREDIENTS: BENZALKONIUM CHLORIDE 0.13 g/100 g
INACTIVE INGREDIENTS: PHENOXYETHANOL; POTASSIUM SORBATE; SODIUM BENZOATE; POLYSORBATE 20; CITRIC ACID MONOHYDRATE; .ALPHA.-TOCOPHEROL; WATER; ALOE VERA LEAF

Drug Facts

Active ingredient

Benzalkonium chloride 0.13%

Purpose

Antimicrobial

Uses

- For hand sanitizing to decrease bacteria on the skin
- Recommended for repeated use

Warnings

For external use only

When using this product

avoid contact with eyes. In case of eye contact, flush eyes with water.

Stop use and ask a doctor

If irritation or redness develops, or if condition persists for more than 72 hours.

Keep out of reach of children

If swallowed, get medical help or contact a Poison Control Center right away.

Directions

- take wipe and rub thoroughly over all surfaces of both hands. Wet hands thoroughly with wipe
- rub hands together briskly to dry without wiping
- dispose of wipe
- do not flush

Other information

Store between 15°-30°C (59°F - 86°F).

Avoid freezing and excessive heat above 40°C (104°F)

Inactive ingredients

Purified Water, Aloe Barbadensis Leaf Extract, Citric Acid, Fragrance, Phenoxyethanol, Polysorbate 20, Potassium Sorbate, Sodium Benzoate, Vitamin E

Principal Display Panel

73030-025-01

ANTI-BACTERIAL WIPES

SMELLS AMAZING • SOFTENS HANDS

10 BIG WIPES

KILLS 99.9% OF GERMS

DO NOT FLUSH